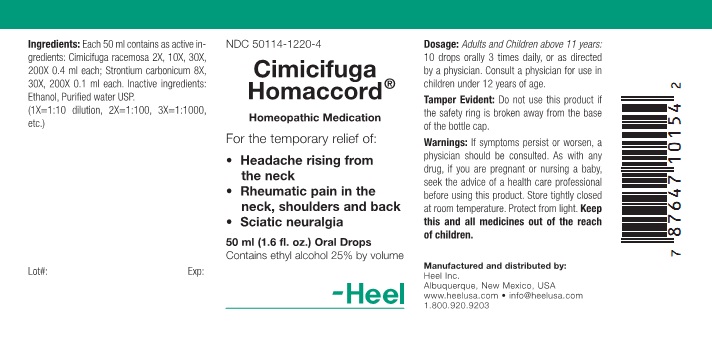 DRUG LABEL: Cimicifuga Homaccord
NDC: 50114-1220 | Form: LIQUID
Manufacturer: Heel Inc
Category: homeopathic | Type: HUMAN OTC DRUG LABEL
Date: 20120228

ACTIVE INGREDIENTS: BLACK COHOSH 2 [hp_X]/50 mL; STRONTIUM CARBONATE 8 [hp_X]/50 mL
INACTIVE INGREDIENTS: ALCOHOL; WATER

Cimicifuga Homaccord Oral Drop

KEEP OUT OF REACH OF CHILDREN

Keep this and all medicines out of the reach of children.

INDICATIONS AND USAGE

For the temporary relief of:

- Headache rising from the neck
- Rheumatic pain in the neck, shoulders and back
- Sciatic neuralgia

WARNINGS

If symptoms persist or worsen, a physician should be consulted. As with any drug, if you are pregnant or nursing a baby, seek the advise of a health care professional before using this product.

DOSAGE AND ADMINISTRATION

Adults and children above 11 years: 10 drops orally, 3 times daily, or as directed by a physician. Consult a physician for use in children under 12 years of age.

ACTIVE INGREDIENT

Each 50 ml contains as active ingredients: Cimicifuga racemosa 2X, 10X, 30X, 200X 0.4 ml each; Strontium carbonicum 8X, 30X, 200X 0.1 ml each.

INACTIVE INGREDIENT

Inactive ingredients: Ethanol, Purified Water USP.

PURPOSE

Headache rising from the neck, Rheumatic pain in the neck, shoulders and back, Sciatic neuralgia